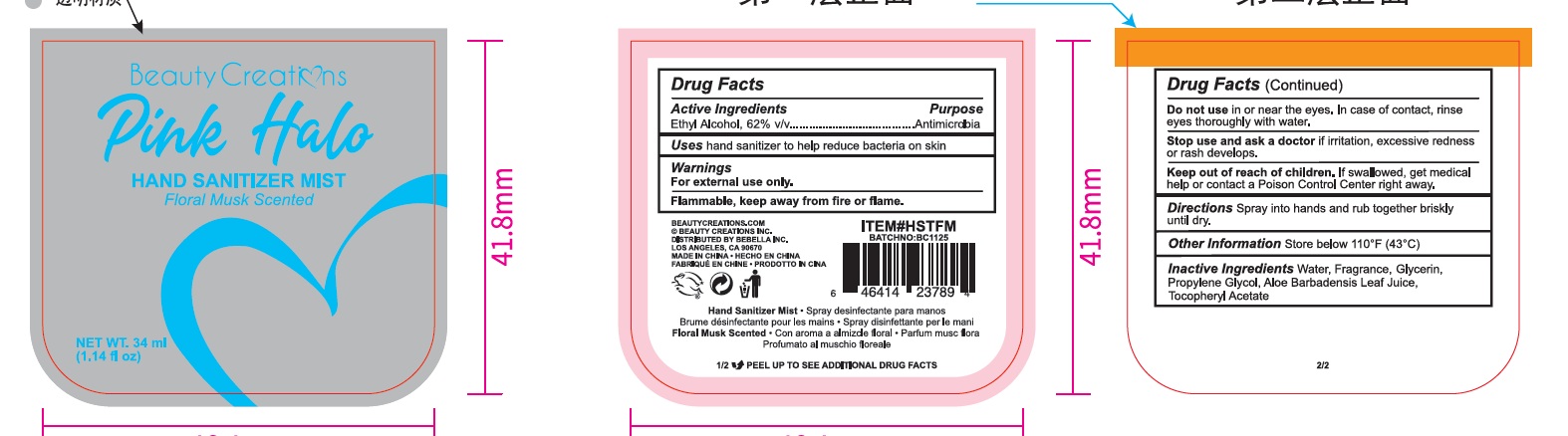 DRUG LABEL: Beauty Creations Pink Halo Hand Sanitizer Mist
NDC: 43473-093 | Form: SPRAY
Manufacturer: Nantong Health & Beyond Hygienic Products Inc.
Category: otc | Type: HUMAN OTC DRUG LABEL
Date: 20260104

ACTIVE INGREDIENTS: ALCOHOL 62 mL/100 mL
INACTIVE INGREDIENTS: WATER; GLYCERIN; PROPYLENE GLYCOL; .ALPHA.-TOCOPHEROL ACETATE; ALOE ARBORESCENS LEAF JUICE

43473-093, Beauty Creations Pink Halo Hand Sanitizer Mist

Active ingredient

Ethyl Alcohol, 62%

Purpose Antimicrobial

Uses

Hand sanitizer to help reduce bacteria on skin

Warnings

For external use only.

Flammable, keep away from fire or flame.

Do not usein or near the eyes. In case of contact, rinse eyes thoroughly with water

Stop use and ask a doctorif irritation, excessive redness, or rash develops

Keep out of reach of children. If swallowed, get medical help or contact a Poison Control Center right away

Directions

Spray into hands and rub together briskly until dry

Other information

Store below 110F (43C)

Inactive ingredients

Water, Fragrance, Glycerin, Propylene Glycol, Aloe Barbadensis Leaf Juice, Tocopheryl Acetate